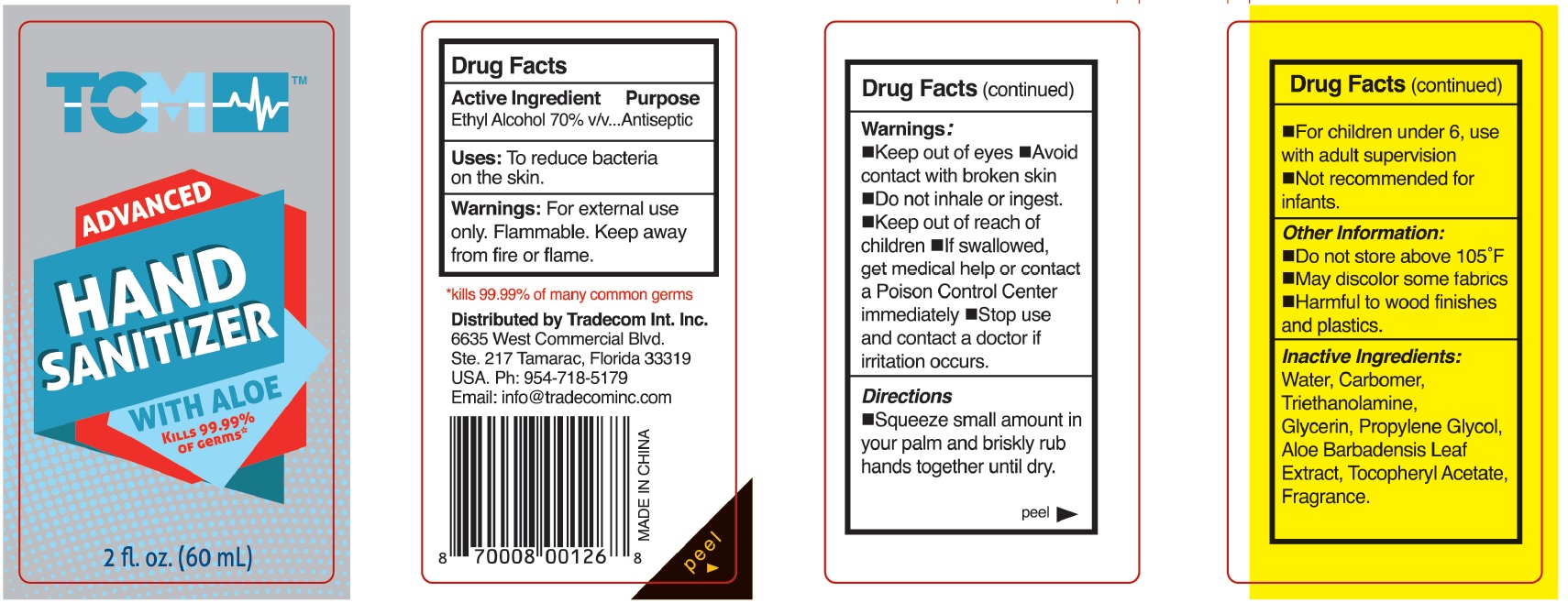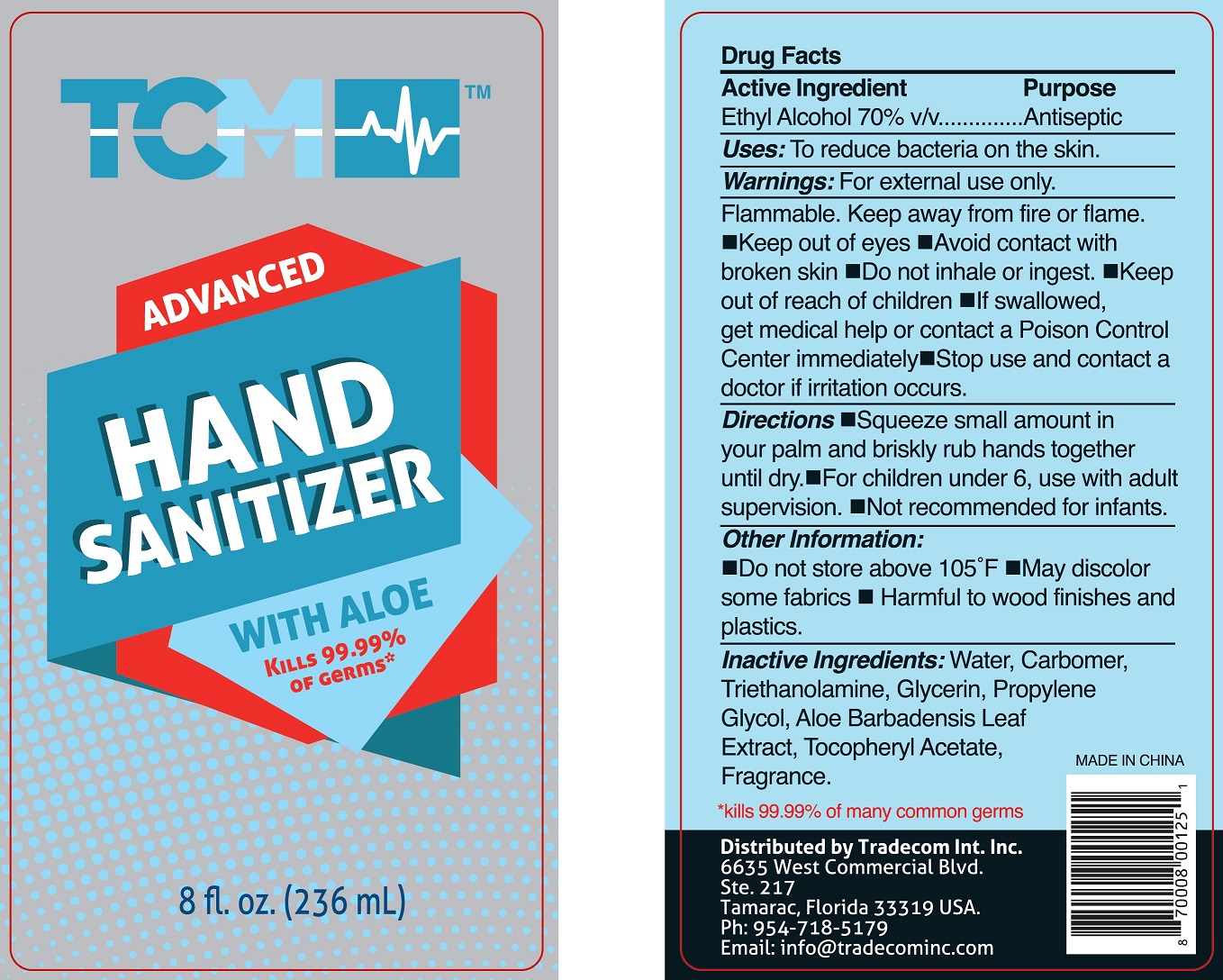 DRUG LABEL: TCM Brand Hand Sanitizer
NDC: 77952-003 | Form: GEL
Manufacturer: Tradecom International, Inc
Category: otc | Type: HUMAN OTC DRUG LABEL
Date: 20200521

ACTIVE INGREDIENTS: ALCOHOL 0.7 mL/1 mL
INACTIVE INGREDIENTS: WATER; CARBOMER HOMOPOLYMER, UNSPECIFIED TYPE; TROLAMINE; GLYCERIN; PROPYLENE GLYCOL; ALOE VERA LEAF; .ALPHA.-TOCOPHEROL ACETATE

TCM Brand Hand Sanitizer

Active Ingredient

Ethyl Alcohol 70% v/v

Purpose

Antiseptic

Uses:

To reduce bacteria on the skin.

Warnings:

For external use only. Flammable. Keep away from fire or flame.

- Keep out of eyes
- Avoid contact with broken skin
- Do not inhale or ingest.

Keep out of reach of children

If swallowed, get medical help or contact a Poison Control Center immediately

Stop use and contact a doctor

if irritation occurs.

Directions

- Squeeze small amount in your palm and briskly rub hands together until dry.
- For children under 6, use with adult supervision
- Not recommended for infants.

Other Information:

- Do not store above 105°F
- May discolor some fabrics
- Harmful to wood finishes and plastics.

Inactive Ingredients:

Water, Carbomer, Triethanolamine, Glycerin, Propylene Glycol, Aloe Barbadensis Leaf Extract, Tocopheryl Acetate, Fragrance.